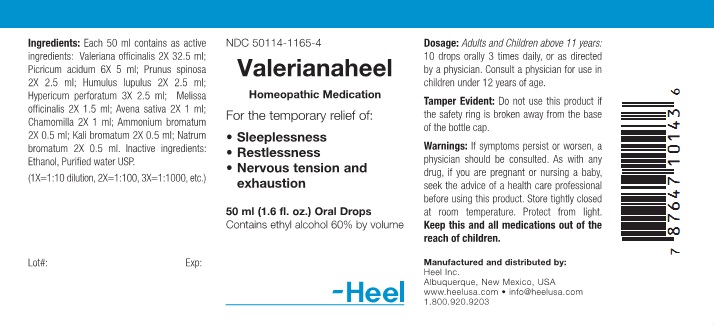 DRUG LABEL: Valerianaheel
NDC: 50114-1165 | Form: LIQUID
Manufacturer: Heel Inc
Category: homeopathic | Type: HUMAN OTC DRUG LABEL
Date: 20120220

ACTIVE INGREDIENTS: VALERIAN 2 [hp_X]/50 mL; TRINITROPHENOL 6 [hp_X]/50 mL; PRUNUS SPINOSA FLOWER BUD 2 [hp_X]/50 mL; HOPS 2 [hp_X]/50 mL; HYPERICUM PERFORATUM 3 [hp_X]/50 mL; MELISSA OFFICINALIS 2 [hp_X]/50 mL; AVENA SATIVA FLOWERING TOP 2 [hp_X]/50 mL; MATRICARIA RECUTITA 2 [hp_X]/50 mL; AMMONIUM BROMIDE 2 [hp_X]/50 mL; POTASSIUM BROMIDE 2 mm/50 mL; SODIUM BROMIDE 2 [hp_X]/50 mL
INACTIVE INGREDIENTS: ALCOHOL; WATER

Valerianaheel Oral Drop

KEEP OUT OF REACH OF CHILDREN

Keep this and all medicines out of the reach of children.

INDICATIONS AND USAGE

For the temporary relief of:

- Sleeplessness
- Restlessness
- Nervous tension and exhaustion

WARNINGS

If symptoms persist or worsen, a physician should be consulted. As with any drug, if you are pregnant or nursing a baby, seek the advise of a health care professional before using this product.

DOSAGE AND ADMINISTRATION

Adults and children above 11 years: 10 drops orally, 3 times daily, or as directed by a physician. Consult a physician for use in children under 12 years of age.

ACTIVE INGREDIENT

Each 50 ml contains as active ingredients: Valeriana officinalis 2X 32.5 ml; Picricum acidum 6X 5 ml; Prunus spinosa 2X 2.5 ml; Humulus lupulus 2X 2.5 ml; Hypericum perforatum 3X 2.5 ml; Melissa officinalis 2X 1.5 ml; Avena sativa 2X 1 ml; Chamomilla 2X 1 ml; Ammonium bromatum 2X 0.5 ml; Kali bromatum 2X 0.5 ml; Natrum bromatum 2X 0.5 ml.

INACTIVE INGREDIENT

Inactive ingredients: Ethanol, Purified Water USP.

PURPOSE

Sleeplessness, Restlessness, Nervous tension and exhaustion